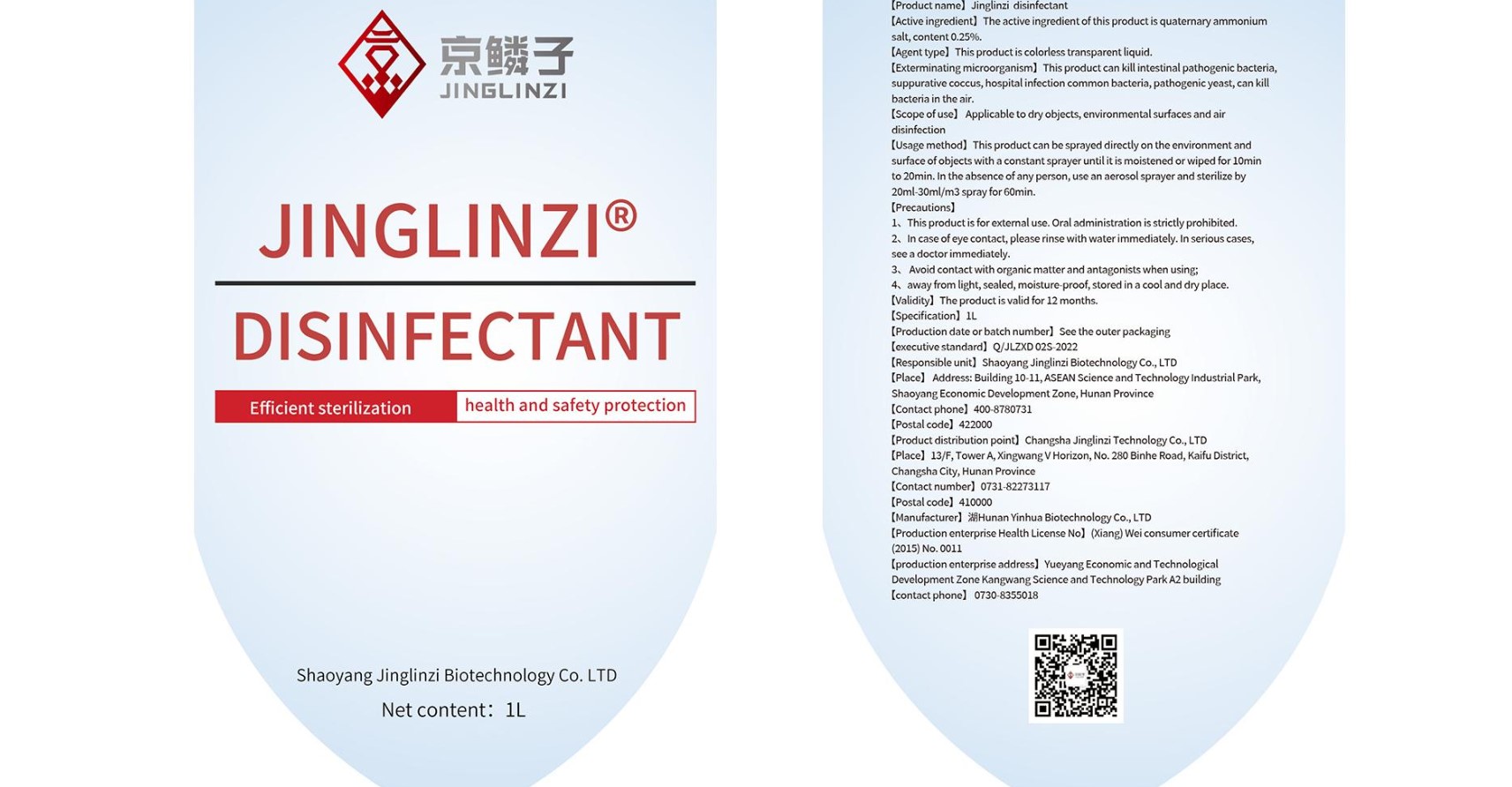 DRUG LABEL: Jinlingzi disinfectant
NDC: 83179-002 | Form: LIQUID
Manufacturer: Shaoyang Jinglinzi Biotechnology Co., Ltd
Category: otc | Type: HUMAN OTC DRUG LABEL
Date: 20230214

ACTIVE INGREDIENTS: BENZALKONIUM CHLORIDE 0.25 g/100 mL
INACTIVE INGREDIENTS: WATER

Jinglinzi disinfectant

ACTIVE INGREDIENT

Quaternary ammonium salt 0.25mg/100mL Purpose: Antiseptic

Purpose: Antiseptic

INDICATIONS AND USAGE

Hand Sanitizer to help reduce bacteria that potentially can cause disease. For use when soap and water are not available.Applicable to dry objects, environmental surfaces and air disinfection.

WARNINGS

1.This product if for external use, Oral administration is strictly prohibited.

2.Avoid contact with organic matter and antagonists when using.

DO NOT USE

in children less than 2 months of age
on open skin wounds

When using this product keep out of eyes, ears, and mouth. In case of contact with eyes, rinse eyes thoroughly with water.
Stop use and ask a doctor if irritation or rash occurs. These may be signs of a serious condition.
Keep out of reach of children. If swallowed, get medical help or contact a Poison Control Center right away.

Stop use and ask a doctor if irritation or rash occurs. These may be signs of a serious condition.

Keep out of reach of children. If swallowed, get medical help or contact a Poison Control Center right away.

DOSAGE AND ADMINISTRATION

This product can be sprayed directly on the environment surface of objects with a constant sprayer until it is moistened or wiped for 10min to 20min. In the absence of any person, use an aerosol spayer and sterilize by 20ml-30ml/m3 spray for 60min.

STORAGE AND HANDLING

Away from light,sealed,moisture-proof,stored in a cool and dry place.

INACTIVE INGREDIENT

water

PACKAGE LABEL

1000mL NDC: 83179-002-01